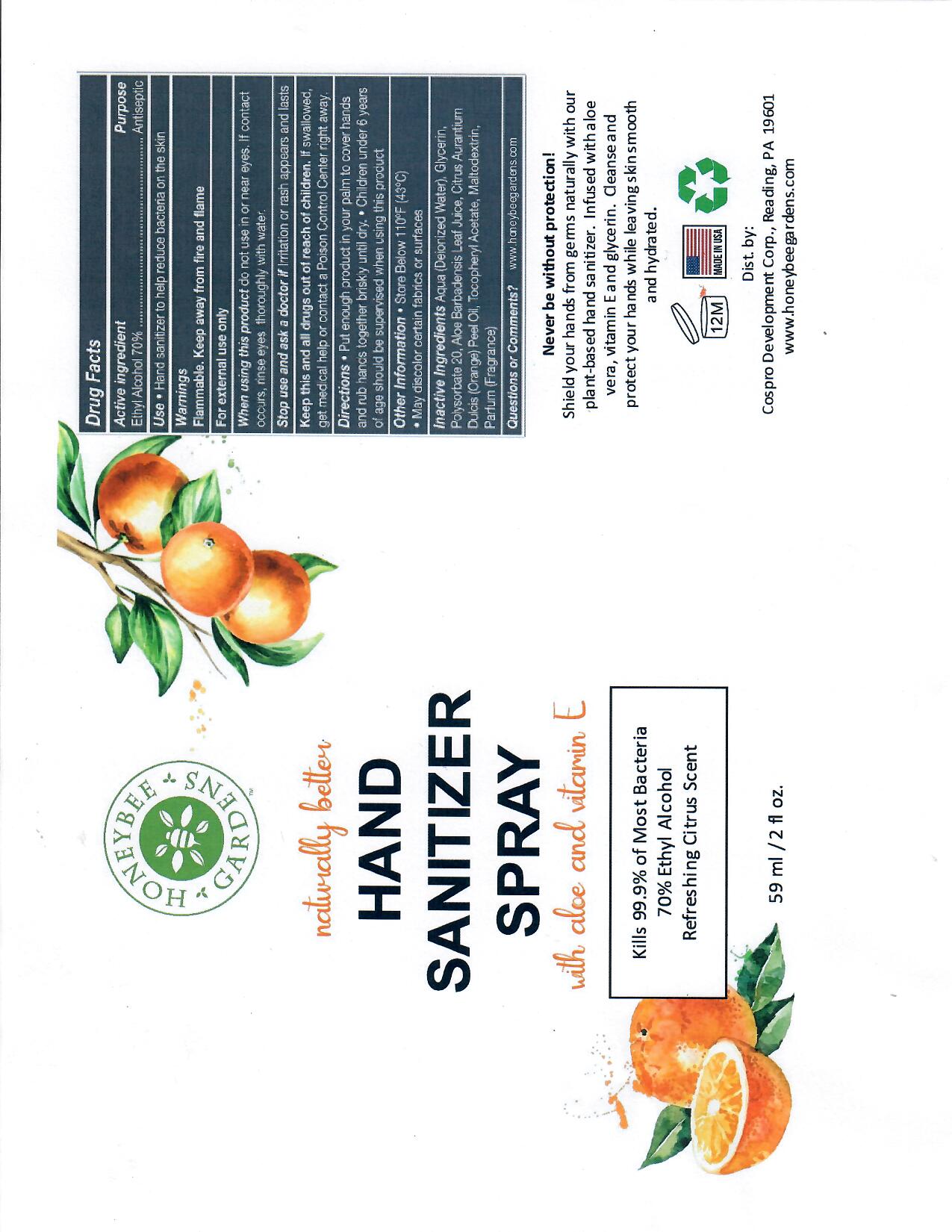 DRUG LABEL: HoneyBeeHandSanitizer
NDC: 46607-120 | Form: SOLUTION
Manufacturer: Cospro Development Corp
Category: otc | Type: HUMAN OTC DRUG LABEL
Date: 20201206

ACTIVE INGREDIENTS: ALCOHOL 70 mL/100 mL
INACTIVE INGREDIENTS: MALTODEXTRIN; ALOE; GLYCERIN; POLYSORBATE 20; WATER; ORANGE PEEL

This is a hand rub manufactured according to the Temporary Policy for Preparation of Certain Alcohol-Based Hand Rub Products During the Public Health Emergency (CoViD-19); Guidance for Industry.

The hand rub is manufactured using only the following United States Pharmacopoeia (USP) grade ingredients in the preparation of the product (percentage in final product formulation) consistent with World Health Organization (WHO) recommendations:

1. Alcohol (ethanol) (USP or Food Chemical Codex (FCC) grade) (70%, volume/volume (v/v)) in an aqueous solution denatured according to Alcohol and Tobacco Tax and Trade Bureau regulations in 27 CFR part 20.
2. Glycerol.
3. Sterile distilled water

Active Ingredient(s)

Ethyl Alcohol 70% v/v. Purpose: Antiseptic

Purpose

Antiseptic, Hand Sanitizer Spray

Use

Hand Sanitizer to help reduce bacteria on the skin.

Warnings

For external use only. Flammable. Keep away from fire and flame

do not use in or near eyes. If contact occurs, rinse eyes thoroughly with water

When using this product do not use in or near eyes. If contact occurs, rinse eyes thoroughly with water.

Stop use and ask a doctor if irritation or rash appears and lasts.

KEEP OUT OF REACH OF CHILDREN

Keep this and all drugs out of reach of children. If swallowed, get medical help or contact a Poison Control Center right away.

Directions

- Put enough product in your palm to cover hands and rub hands together briskly until dry.
- Children under 6 years of age should be supervised when using this product.

Other information

- Store below 110F (43C)
- May discolor certain fabrics or surfaces

Inactive ingredients

deionized water, glycerin, polysorbate 20, aloe barbadensis leaf juice, citrus aurantium dulcis peel oil, tocopheryl acetate, maltodextrin, parfum